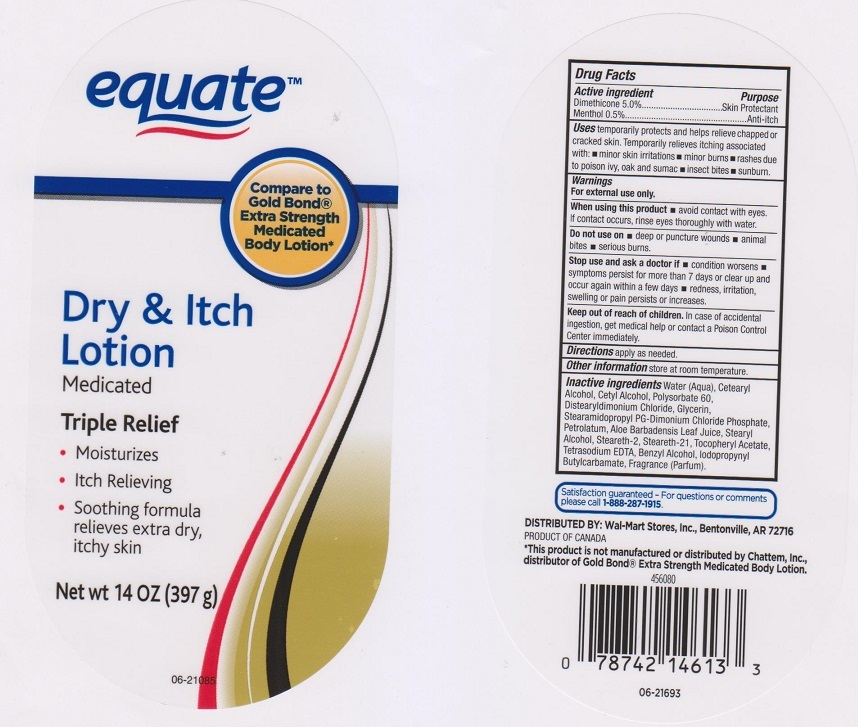 DRUG LABEL: Equate Medicated Dry and Itch
NDC: 49035-333 | Form: LOTION
Manufacturer: Wal-Mart Stores Inc
Category: otc | Type: HUMAN OTC DRUG LABEL
Date: 20170301

ACTIVE INGREDIENTS: DIMETHICONE 0.05 g/1 g; MENTHOL 0.005 g/1 g
INACTIVE INGREDIENTS: WATER; CETOSTEARYL ALCOHOL; CETYL ALCOHOL; POLYSORBATE 60; DISTEARYLDIMONIUM CHLORIDE; GLYCERIN; STEARAMIDOPROPYL PG-DIMONIUM CHLORIDE PHOSPHATE; PETROLATUM; ALOE VERA LEAF; STEARYL ALCOHOL; STEARETH-2; STEARETH-21; .ALPHA.-TOCOPHEROL ACETATE, DL-; EDETATE SODIUM; BENZYL ALCOHOL; IODOPROPYNYL BUTYLCARBAMATE

Drug Facts

Active ingredient

Dimethicone 5%

Purpose

Skin Protectant

Active ingredient

Menthol 0.5%

Purpose

Anti-itch

Uses

temporarily protects and helps relieve chapped or cracked skin. Temporarily relieves itching associated with:

- minor skin irritations
- minor burns
- rashes due to poison ivy, oak and sumac
- insect bites
- sunburn

Warnings

For external use only.

When using this product

- avoid contact with eyes. If contact occurs, rinse eyes thoroughly with water.

Do not use on

- deep or puncture wounds
- animal bites
- serious burns

Stop use and ask a doctor if

- condition worsens
- symptoms persist for more than 7 days or clear up and occur again within a few days
- redness, irritation, swelling or pain persists or increases.

Keep out of reach of children.

In case of accidental ingestion, get medical help or contact a Poison Control Center immediately.

Directions

apply as needed

Other information

store at room temperature.

Inactive ingredients

Water (Aqua), Cetearyl Alcohol, Cetyl Alcohol, Polysorbate 60, Distearyldimonium Chloride, Glycerin, Stearamidopropyl PG-Dimonium Chloride Phosphate, Petrolatum, Aloe Barbadensis Leaf Juice, Stearyl Alcohol, Steareth-2, Steareth-21, Tocopheryl Acetate, Tetrasodium EDTA, Benyzl Alcohol, Iodopropynyl Butylcarbamate, Fragrance (Parfum).